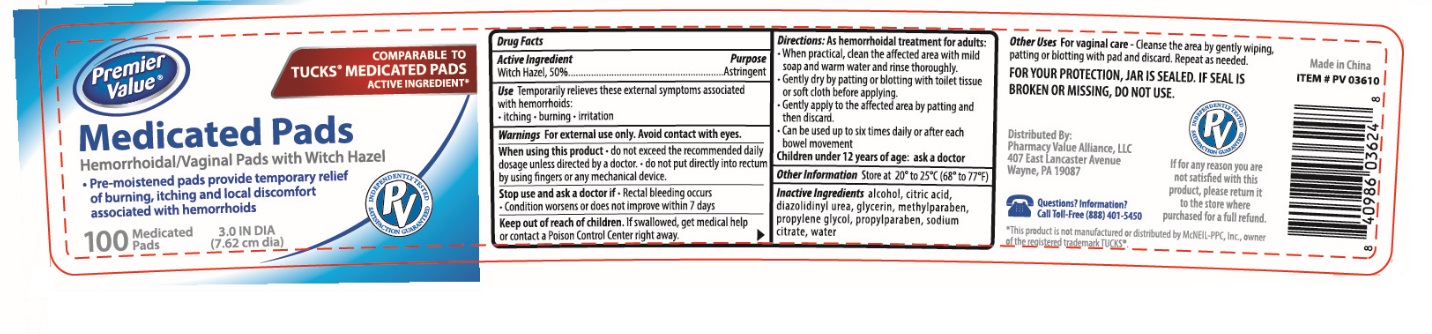 DRUG LABEL: Premier Value Medicated Pads
NDC: 70108-029 | Form: CLOTH
Manufacturer: Ashtel Studios, Inc.
Category: otc | Type: HUMAN OTC DRUG LABEL
Date: 20230120

ACTIVE INGREDIENTS: WITCH HAZEL 0.0086 g/1 1
INACTIVE INGREDIENTS: ALCOHOL; CITRIC ACID MONOHYDRATE; DIAZOLIDINYL UREA; GLYCERIN; METHYLPARABEN; PROPYLENE GLYCOL; PROPYLPARABEN; SODIUM CITRATE, UNSPECIFIED FORM; WATER

Premier Value® Medicated Pads

Active Ingredient

Witch Hazel, 50%

Purpose

Astringent

INDICATIONS AND USAGE

Use Temporarily relieves these external symptoms associated with hemorrhoids:

• itching • burning • irritation

WARNINGS

Warnings For external use only. Avoid contact with eyes.

When using this product • do not exceed the recommended daily dosage unless directed by a doctor. • do not put directly into rectum by using fingers or any mechanical device.

Stop use and ask a doctor if • Rectal bleeding occurs • Condition worsens or does not improve within 7 days

Keep out of reach of children. If swallowed, get medical help or contact a Poison Control Center right away.

DOSAGE AND ADMINISTRATION

Directions: As hemorrhoidal treatments for adults:

• When practical, clean the affected area with mild soap and warm water and rinse thoroughly.

• Gently dry by patting or blotting with toilet tissue or soft cloth before applying.

• Gently apply to the affected area by patting and then discard.

• Can be used up to six times daily or after each bowel movement

Children under 12 years of age: ask a doctor

Other Information Store at 20° to 25°C (68° to 77°F)

INACTIVE INGREDIENT

Inactive Ingredients alcohol, citric acid, diazolidinyl urea, glycerin, methylparaben, propylene glycol, propylparaben, sodium citrate, water

COMPARABLE TO TUCKS® MEDICATED PADS ACTIVE INGREDIENT*

Hemorrhoidal/Vaginal Pads with Witch Hazel

• Pre-moistened pads provide temporary relief of burning, itching and local discomfort associated with hemorrhoids

3.0 IN DIA (7.62 cm dia)

Other Uses For vaginal care - Cleanse the area by gently wiping, patting or blotting with pad and discard. Repeat as needed.

FOR YOUR PROTECTION, JAR IS SEALED. IF SEAL IS BROKEN OR MISSING, DO NOT USE.

Made in China

Distributed By:

Pharmacy Value Alliance, LLC

407 East Lancaster Avenue

Wayne, PA 19087

If for any reason you are not satisfied with this product, please return it to the store where purchased for a full refund.

Questions? Information?

Call Toll-Free (888) 401-5450

*This product is not manufactured or distributed by McNEIL-PPC, Inc, owner of the registered trademark TUCKS®